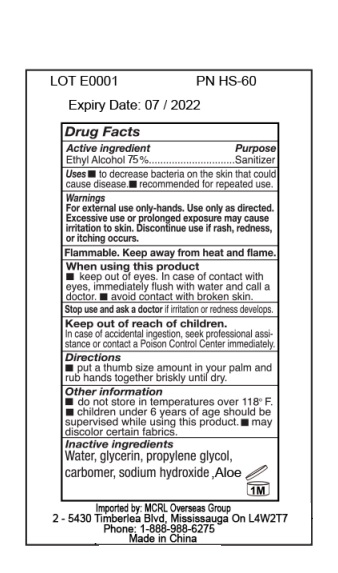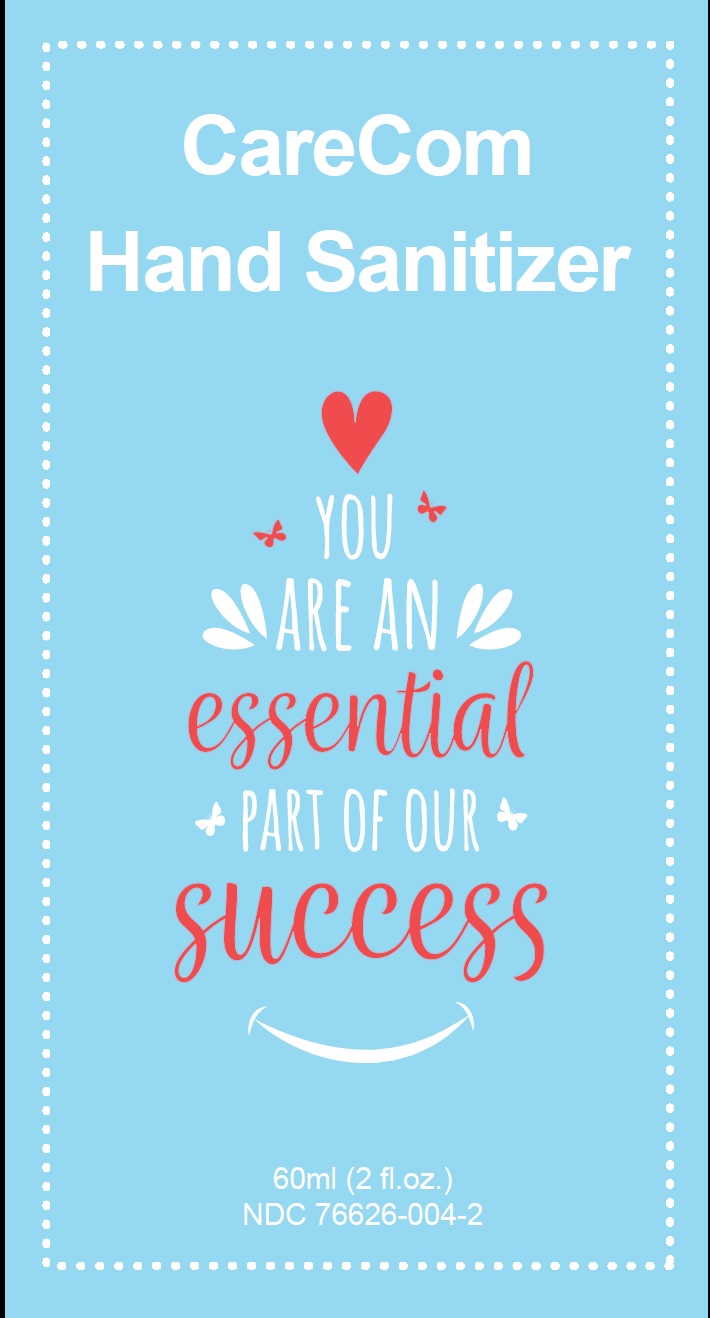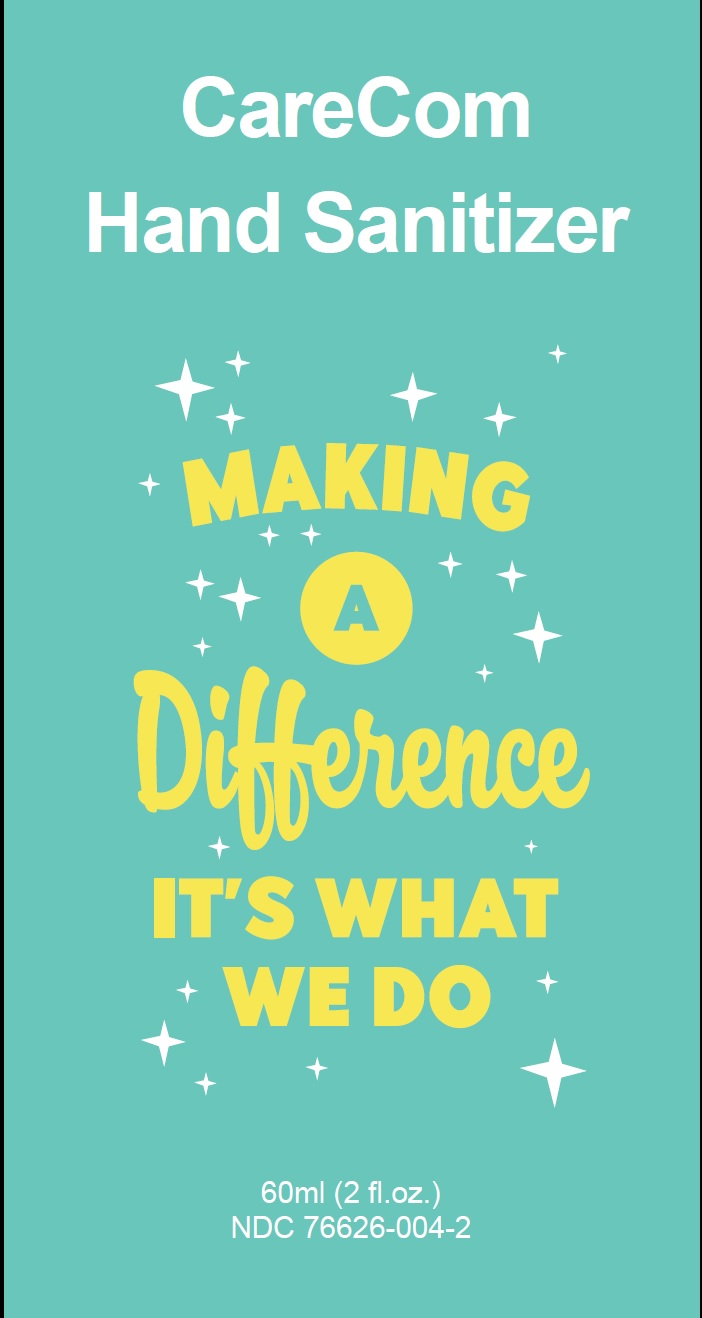 DRUG LABEL: CareCom Hand Sanitizer
NDC: 76626-004 | Form: GEL
Manufacturer: MCRL Overseas Printing Inc
Category: otc | Type: HUMAN OTC DRUG LABEL
Date: 20200817

ACTIVE INGREDIENTS: ALCOHOL 75 mL/100 mL
INACTIVE INGREDIENTS: WATER; GLYCERIN; PROPYLENE GLYCOL; CARBOMER HOMOPOLYMER, UNSPECIFIED TYPE; SODIUM HYDROXIDE; ALOE

Active Ingredient

Ethyl Alcohol 75% v/v

Purpose

Sanitizer

Use

To decrease bacteria on the skin that could cause disease. Recommended for repeated use.

Warnings

For external use only-hands. Use only as directed. Excessive use or prolonged exposure may cause irritation to skin. Discontinue use if rash, redness or itching appears. Flammable. Keep away from heat or flame.

When using this product

- keep out of eyes. In case of contact with eyes, immediately flush with water and call a doctor.
- avoid contact with broken skin.

Stop use and ask a doctor if irritation or redness develops.

Keep out of reach of children. In case of accidental ingestion seek professional assistance or contact a poison control center immedietly.

Directions

Put a thumb size amount in your palm and rub hands together briskly until dry.

Other information:

- do not store in temperature over 118F.
- children under the 6 years of age should be supervised while using this product.
- may discolor certain fabrics.

Inactive ingredients

Water, glycerin, propylene Glycol, carbomer, sodium hydroxide, Aloe